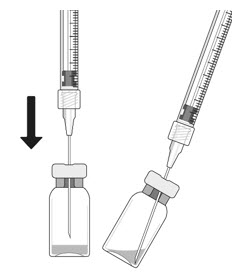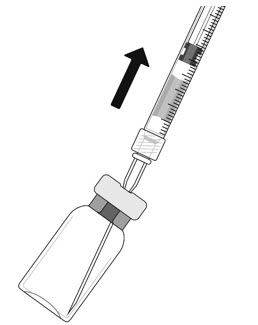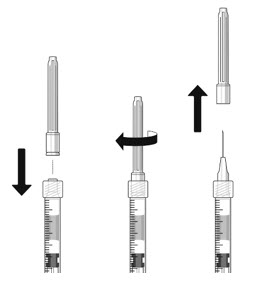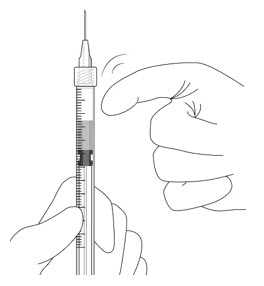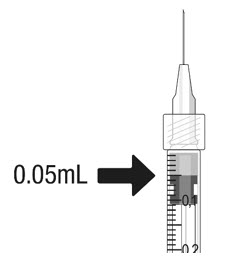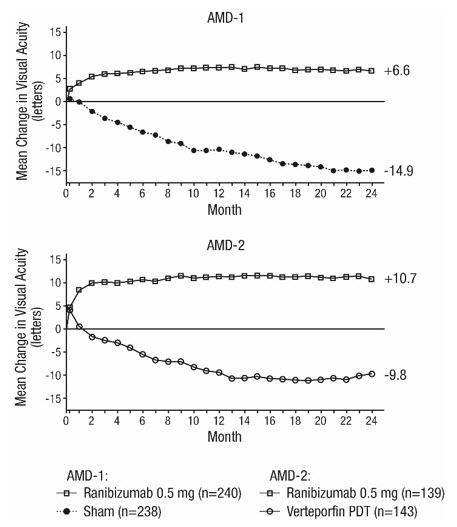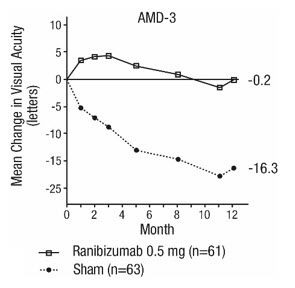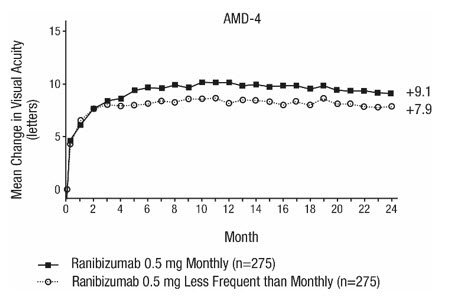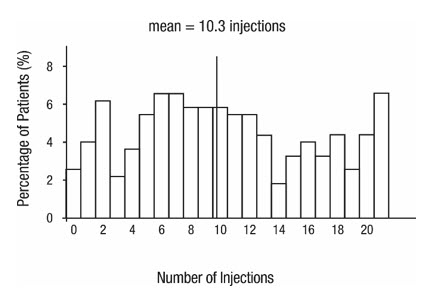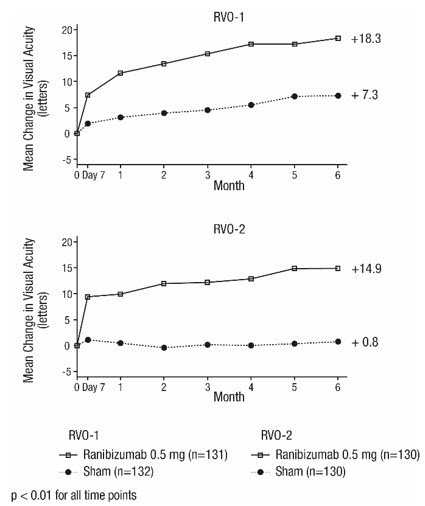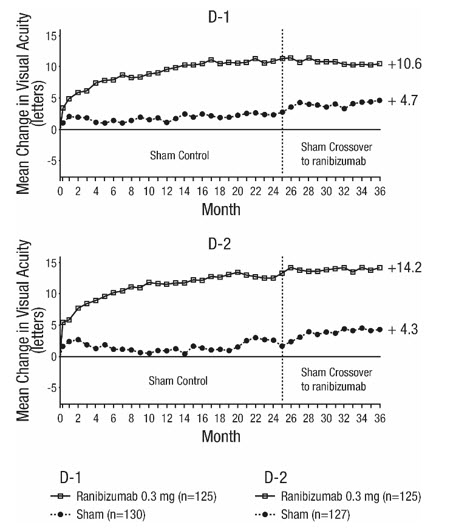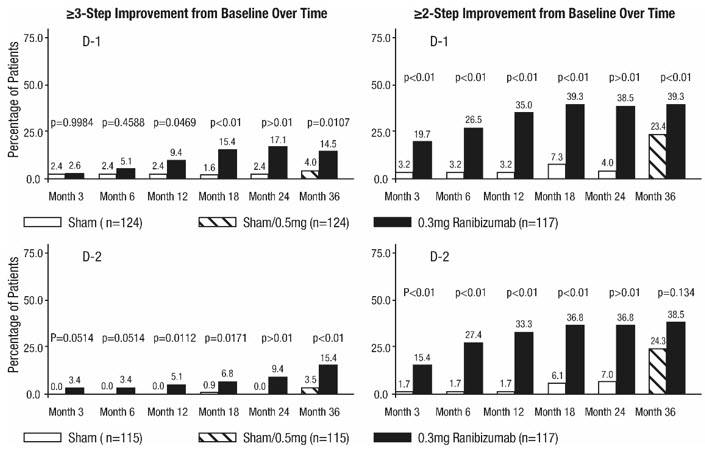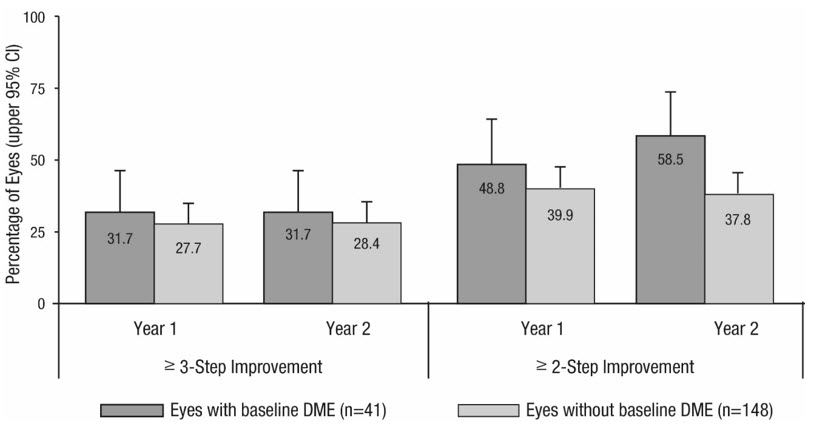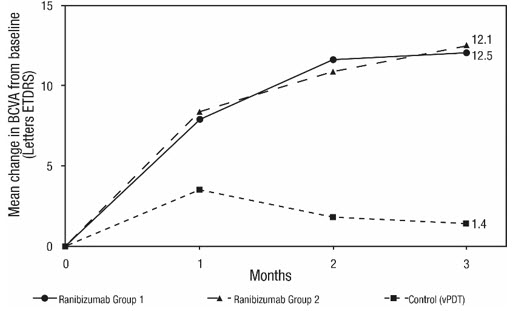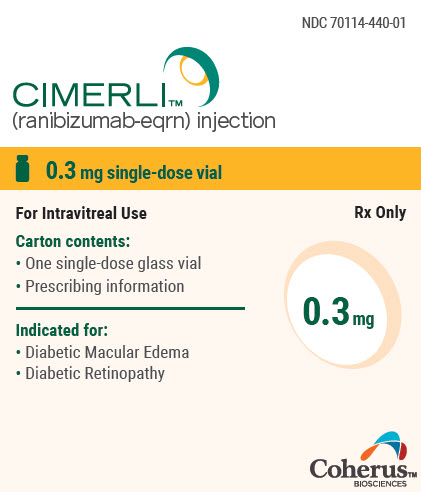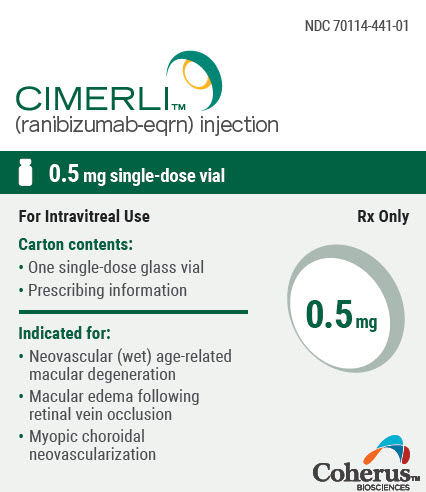 DRUG LABEL: CIMERLI
NDC: 70114-440 | Form: INJECTION, SOLUTION
Manufacturer: Coherus BioSciences Inc
Category: prescription | Type: HUMAN PRESCRIPTION DRUG LABEL
Date: 20250507

ACTIVE INGREDIENTS: RANIBIZUMAB 0.3 mg/0.05 mL
INACTIVE INGREDIENTS: HISTIDINE; HISTIDINE MONOHYDROCHLORIDE MONOHYDRATE; POLYSORBATE 20; WATER

HIGHLIGHTS OF PRESCRIBING INFORMATION

These highlights do not include all the information needed to use CIMERLI safely and effectively. See full prescribing information for CIMERLI.
CIMERLI™ (ranibizumab-eqrn) injection, for intravitreal use
Initial U.S. Approval: 2022
CIMERLI (ranibizumab-eqrn) is biosimilar [Biosimilar means that the biological product is approved based on data demonstrating that it is highly similar to an FDA-approved biological product, known as a reference product, and that there are no clinically meaningful differences between the biosimilar product and the reference product. Biosimilarity of CIMERLI has been demonstrated for the condition(s) of use (e.g., indication(s), dosing regimen(s)), strength(s), dosage form(s), and route(s) of administration described in its Full Prescribing Information.] with LUCENTIS® (ranibizumab injection).

RECENT MAJOR CHANGES

Warnings and Precautions, Retinal Vasculitis with or without Occlusion (5.5) 06/2024

1 INDICATIONS AND USAGE

CIMERLI, a vascular endothelial growth factor (VEGF) inhibitor, is indicated for the treatment of patients with:

- Neovascular (Wet) Age-Related Macular Degeneration (AMD) (1.1)
- Macular Edema Following Retinal Vein Occlusion (RVO) (1.2)
- Diabetic Macular Edema (DME) (1.3)
- Diabetic Retinopathy (DR) (1.4)
- Myopic Choroidal Neovascularization (mCNV) (1.5)

2 DOSAGE AND ADMINISTRATION

For ophthalmic intravitreal injection only (2.1)

- Neovascular (Wet) Age-Related Macular Degeneration (AMD) (2.2):
  CIMERLI 0.5 mg (0.05 mL) is recommended to be administered by intravitreal injection once a month (approximately 28 days).
  - Although not as effective, patients may be treated with 3 monthly doses followed by less frequent dosing with regular assessment.
  - Although not as effective, patients may also be treated with one dose every 3 months after 4 monthly doses. Patients should be assessed regularly.
- Macular Edema Following Retinal Vein Occlusion (RVO) (2.3):
  CIMERLI 0.5 mg (0.05 mL) is recommended to be administered by intravitreal injection once a month (approximately 28 days).
- Diabetic Macular Edema (DME) and Diabetic Retinopathy (DR) (2.4):
  CIMERLI 0.3 mg (0.05 mL) is recommended to be administered by intravitreal injection once a month (approximately 28 days).
- Myopic Choroidal Neovascularization (mCNV) (2.5):
  CIMERLI 0.5 mg (0.05 mL) is recommended to be initially administered by intravitreal injection once a month (approximately 28 days) for up to three months. Patients may be retreated if needed.

3 DOSAGE FORMS AND STRENGTHS

- Single-dose glass vial designed to provide 0.05 mL for intravitreal injections:
  - 10 mg/mL solution (CIMERLI 0.5 mg) (3)
  - 6 mg/mL solution (CIMERLI 0.3 mg) (3)

4 CONTRAINDICATIONS

- Ocular or periocular infections (4.1)
- Hypersensitivity (4.2)

5 WARNINGS AND PRECAUTIONS

- Endophthalmitis and retinal detachments may occur following intravitreal injections. Patients should be monitored following the injection (5.1).
- Increases in intraocular pressure (IOP) have been noted both pre- and post-intravitreal injection (5.2).
- There is a potential risk of arterial thromboembolic events following intravitreal use of VEGF inhibitors (5.3).
- Fatal events occurred more frequently in patients with DME and DR at baseline, who were treated monthly with ranibizumab compared with control (5.4).

6 ADVERSE REACTIONS

The most common adverse reactions (reported more frequently in ranibizumab-treated subjects than control subjects) are conjunctival hemorrhage, eye pain, vitreous floaters, and increased IOP (6.2).

To report SUSPECTED ADVERSE REACTIONS, contact Coherus BioSciences at 1-800-483-3692 or FDA at 1-800-FDA-1088 or www.fda.gov/medwatch.

FULL PRESCRIBING INFORMATION

1 INDICATIONS AND USAGE

CIMERLI is indicated for the treatment of patients with:

2 DOSAGE AND ADMINISTRATION

2.1 General Dosing Information

FOR OPHTHALMIC INTRAVITREAL INJECTION.

Vials: A 5-micron sterile filter needle (19-gauge × 1-1/2 inch), a 1-mL Luer lock syringe and a 30-gauge × 1/2 inch sterile injection needle are needed but not included.

2.2 Neovascular (Wet) Age-Related Macular Degeneration (AMD)

CIMERLI 0.5 mg (0.05 mL of 10 mg/mL solution) is recommended to be administered by intravitreal injection once a month (approximately 28 days).

Although not as effective, patients may be treated with 3 monthly doses followed by less frequent dosing with regular assessment. In the 9 months after three initial monthly doses, less frequent dosing with 4-5 doses on average is expected to maintain visual acuity while monthly dosing may be expected to result in an additional average 1-2 letter gain. Patients should be assessed regularly [see Clinical Studies (14.1)] .

Although not as effective, patients may also be treated with one dose every 3 months after 4 monthly doses. Compared with continued monthly dosing, dosing every 3 months over the next 9 months will lead to an approximate 5-letter (1-line) loss of visual acuity benefit, on average. Patients should be assessed regularly [see Clinical Studies (14.1)] .

2.3 Macular Edema Following Retinal Vein Occlusion (RVO)

CIMERLI 0.5 mg (0.05 mL of 10 mg/mL solution) is recommended to be administered by intravitreal injection once a month (approximately 28 days).

In Studies RVO-1 and RVO-2, patients received monthly injections of ranibizumab for 6 months. In spite of being guided by optical coherence tomography and visual acuity re-treatment criteria, patients who were then not treated at Month 6 experienced on average, a loss of visual acuity at Month 7, whereas patients who were treated at Month 6 did not. Patients should be treated monthly [see Clinical Studies (14.2)] .

2.4 Diabetic Macular Edema (DME) and Diabetic Retinopathy (DR)

CIMERLI 0.3 mg (0.05 mL of 6 mg/mL solution) is recommended to be administered by intravitreal injection once a month (approximately 28 days).

2.5 Myopic Choroidal Neovascularization (mCNV)

CIMERLI 0.5 mg (0.05 mL of 10 mg/mL solution) is recommended to be initially administered by intravitreal injection once a month (approximately 28 days) for up to 3 months. Patients may be retreated if needed [(see Clinical Studies 14.5)] .

2.6 Preparation for Administration

Vial:

Using aseptic technique, all of the CIMERLI vial contents are withdrawn through a 5-micron (19-gauge × 1-1/2 inch), sterile filter needle attached to a 1 mL syringe (not included). The filter needle should be discarded after withdrawal of the vial contents and should not be used for intravitreal injection. The filter needle should be replaced with a sterile 30-gauge × 1/2 inch needle for the intravitreal injection.

Use aseptic technique to carry out the following preparation steps:

1. Prepare for intravitreal injection with the following medical devices for use in a single eye (not included):
  - a 5-micron sterile filter needle (19-gauge × 1-1/2 inch)
  - a 1 mL sterile Luer lock syringe (with marking to measure 0.05 mL)
  - a sterile injection needle (30-gauge × 1/2-inch)
2. Before withdrawal, disinfect the outer part of the rubber stopper of the vial.
3. Place a 5-micron filter needle (19-gauge × 1-1/2 inch) onto a 1 mL Luer lock syringe using aseptic technique.
4. Push the filter needle into the center of the vial stopper until the needle touches the bottom edge of the vial.
5. Withdraw all the liquid from the vial, keeping the vial in an upright position, slightly inclined to ease complete withdrawal.
6. Ensure that the plunger rod is drawn sufficiently back when emptying the vial in order to completely empty the filter needle.
7. The filter needle should be discarded after withdrawal of the vial contents and must not be used for the intravitreal injection.
8. Attach a 30-gauge × 1/2-inch sterile injection needle firmly onto the syringe by screwing it tightly onto the Luer lock. Carefully remove the needle cap by pulling it straight off. Do not wipe the needle at any time.
9. Hold the syringe with the needle pointing up. If there are any air bubbles, gently tap the syringe with your finger until the bubbles rise to the top.
10. Hold the syringe at eye level, and carefully push the plunger rod until the plunger tip is aligned with the line that marks 0.05 mL on the syringe.

2.7 Administration

The intravitreal injection procedure should be carried out under controlled aseptic conditions, which include the use of sterile gloves, a sterile drape, and a sterile eyelid speculum (or equivalent). Adequate anesthesia and a broad-spectrum microbicide should be given prior to the injection.

Prior to and 30 minutes following the intravitreal injection, patients should be monitored for elevation in intraocular pressure using tonometry. Monitoring may also consist of a check for perfusion of the optic nerve head immediately after the injection [see Warnings and Precautions (5.2)] . Patients should also be monitored for and instructed to report any symptoms suggestive of endophthalmitis without delay following the injection [see Warnings and Precautions (5.1)] .

Each vial should only be used for the treatment of a single eye. If the contralateral eye requires treatment, a new vial should be used and the sterile field, syringe, gloves, drapes, eyelid speculum, filter needle, and injection needles should be changed before CIMERLI is administered to the other eye.

No special dosage modification is required for any of the populations that have been studied (e.g., gender, elderly).

3 DOSAGE FORMS AND STRENGTHS

Single-dose glass vial designed to provide 0.05 mL for intravitreal injection.

- Colorless to pale yellow 10 mg/mL solution (0.5 mg)
- Colorless to pale yellow 6 mg/mL solution (0.3 mg)

4 CONTRAINDICATIONS

4.1 Ocular or Periocular Infections

CIMERLI is contraindicated in patients with ocular or periocular infections.

4.2 Hypersensitivity

CIMERLI is contraindicated in patients with known hypersensitivity to ranibizumab products or any of the excipients in CIMERLI. Hypersensitivity reactions may manifest as severe intraocular inflammation.

5 WARNINGS AND PRECAUTIONS

5.1 Endophthalmitis and Retinal Detachments

Intravitreal injections, including those with ranibizumab products, have been associated with endophthalmitis and retinal detachments. Proper aseptic injection technique should always be used when administering CIMERLI. In addition, patients should be monitored following the injection to permit early treatment should an infection occur [see Dosage and Administration (2.6, 2.7) and Patient Counseling Information (17)] .

5.2 Increases in Intraocular Pressure

Increases in intraocular pressure have been noted both pre-injection and post-injection (at 60 minutes) while being treated with ranibizumab products. Monitor intraocular pressure prior to and following intravitreal injection with CIMERLI and manage appropriately [see Dosage and Administration (2.7)] .

5.3 Thromboembolic Events

Although there was a low rate of arterial thromboembolic events (ATEs) observed in the ranibizumab clinical trials, there is a potential risk of ATEs following intravitreal use of VEGF inhibitors. Arterial thromboembolic events are defined as nonfatal stroke, nonfatal myocardial infarction, or vascular death (including deaths of unknown cause).

Neovascular (Wet) Age-Related Macular Degeneration

The ATE rate in the three controlled neovascular AMD studies (AMD-1, AMD-2, AMD-3) during the first year was 1.9% (17 of 874) in the combined group of patients treated with 0.3 mg or 0.5 mg ranibizumab compared with 1.1% (5 of 441) in patients from the control arms [see Clinical Studies (14.1)] . In the second year of Studies AMD-1 and AMD-2, the ATE rate was 2.6% (19 of 721) in the combined group of ranibizumab-treated patients compared with 2.9% (10 of 344) in patients from the control arms. In Study AMD-4, the ATE rates observed in the 0.5 mg arms during the first and second year were similar to rates observed in Studies AMD-1, AMD-2, and AMD-3.

In a pooled analysis of 2-year controlled studies [AMD-1, AMD-2, and a study of ranibizumab used adjunctively with verteporfin photodynamic therapy (PDT)], the stroke rate (including both ischemic and hemorrhagic stroke) was 2.7% (13 of 484) in patients treated with 0.5 mg ranibizumab compared to 1.1% (5 of 435) in patients in the control arms [odds ratio 2.2 (95% confidence interval (0.8-7.1)].

Macular Edema Following Retinal Vein Occlusion

The ATE rate in the two controlled RVO studies during the first 6 months was 0.8% in both the ranibizumab and control arms of the studies (4 of 525 in the combined group of patients treated with 0.3 mg or 0.5 mg ranibizumab and 2 of 260 in the control arms) [see Clinical Studies (14.2)] . The stroke rate was 0.2% (1 of 525) in the combined group of ranibizumab-treated patients compared to 0.4% (1 of 260) in the control arms.

Diabetic Macular Edema and Diabetic Retinopathy

Safety data are derived from studies D-1 and D-2. All enrolled patients had DME and DR at baseline [see Clinical Studies (14.3, 14.4)] .

In a pooled analysis of Studies D-1 and D-2 [see Clinical Studies (14.3)] , the ATE rate at 2 years was 7.2% (18 of 250) with 0.5 mg ranibizumab, 5.6% (14 of 250) with 0.3 mg ranibizumab, and 5.2% (13 of 250) with control. The stroke rate at 2 years was 3.2% (8 of 250) with 0.5 mg ranibizumab, 1.2% (3 of 250) with 0.3 mg ranibizumab, and 1.6% (4 of 250) with control. At 3 years, the ATE rate was 10.4% (26 of 249) with 0.5 mg ranibizumab and 10.8% (27 of 250) with 0.3 mg ranibizumab; the stroke rate was 4.8% (12 of 249) with 0.5 mg ranibizumab and 2.0% (5 of 250) with 0.3 mg ranibizumab.

5.4 Fatal Events in Patients with Diabetic Macular Edema and Diabetic Retinopathy at Baseline

Diabetic Macular Edema and Diabetic Retinopathy

Safety data are derived from studies D-1 and D-2. All enrolled patients had DME and DR at baseline [see Clinical Studies (14.3, 14.4)] .

A pooled analysis of Studies D-1 and D-2 [see Clinical Studies (14.3)] , showed that fatalities in the first 2 years occurred in 4.4% (11 of 250) of patients treated with 0.5 mg ranibizumab, in 2.8% (7 of 250) of patients treated with 0.3 mg ranibizumab, and in 1.2% (3 of 250) of control patients. Over 3 years, fatalities occurred in 6.4% (16 of 249) of patients treated with 0.5 mg ranibizumab and in 4.4% (11 of 250) of patients treated with 0.3 mg ranibizumab. Although the rate of fatal events was low and included causes of death typical of patients with advanced diabetic complications, a potential relationship between these events and intravitreal use of VEGF inhibitors cannot be excluded.

5.5 Retinal Vasculitis with or without Occlusion

Retinal vasculitis with or without occlusion, typically in the presence of preexisting intraocular inflammation or post-treatment with other intravitreal agents, have been reported with the use of ranibizumab products. Discontinue treatment with CIMERLI in patients who develop these events. Patients should be instructed to report any change in vision without delay [see Patient Counseling Information (17)].

6 ADVERSE REACTIONS

The following adverse reactions are discussed in greater detail in other sections of the label:

- Endophthalmitis and Retinal Detachments [see Warnings and Precautions (5.1)]
- Increases in Intraocular Pressure [see Warnings and Precautions (5.2)]
- Thromboembolic Events [see Warnings and Precautions (5.3)]
- Fatal Events in patients with DME and DR at baseline [see Warnings and Precautions (5.4)]

6.1 Injection Procedure

Serious adverse reactions related to the injection procedure have occurred in < 0.1% of intravitreal injections, including endophthalmitis [see Warnings and Precautions (5.1)] , rhegmatogenous retinal detachment, and iatrogenic traumatic cataract.

6.2 Clinical Trials Experience

Because clinical trials are conducted under widely varying conditions, adverse reaction rates observed in the clinical trials of a drug cannot be directly compared to rates in the clinical trials of another drug and may not reflect the rates observed in practice.

The data below reflect exposure to 0.5 mg ranibizumab in 440 patients with neovascular AMD in Studies AMD-1, AMD-2, and AMD-3; in 259 patients with macular edema following RVO. The data also reflect exposure to 0.3 mg ranibizumab in 250 patients with DME and DR at baseline [see Clinical Studies (14)] .

Safety data observed in 224 patients with mCNV, as well as Studies AMD-4 and D-3, were consistent with these results. On average, the rates and types of adverse reactions in patients were not significantly affected by dosing regimen.

Ocular Reactions

Table 1 shows frequently reported ocular adverse reactions in ranibizumab-treated patients compared with the control group.

Table 1 Ocular Reactions in the DME and DR, AMD, and RVO Studies
Adverse Reaction | DME and DR 2-year |  | AMD 2-year |  | AMD 1-year |  | RVO 6-month
Adverse Reaction | Ranibizumab 0.3 mg | Control | Ranibizumab 0.5 mg | Control | Ranibizumab 0.5 mg | Control | Ranibizumab 0.5 mg | Control
Adverse Reaction | n=250 | n=250 | n=379 | n=379 | n=440 | n=441 | n=259 | n=260
Conjunctival hemorrhage | 47% | 32% | 74% | 60% | 64% | 50% | 48% | 37%
Eye pain | 17% | 13% | 35% | 30% | 26% | 20% | 17% | 12%
Vitreous floaters | 10% | 4% | 27% | 8% | 19% | 5% | 7% | 2%
Intraocular pressure increased | 18% | 7% | 24% | 7% | 17% | 5% | 7% | 2%
Vitreous detachment | 11% | 15% | 21% | 19% | 15% | 15% | 4% | 2%
Intraocular inflammation | 4% | 3% | 18% | 8% | 13% | 7% | 1% | 3%
Cataract | 28% | 32% | 17% | 14% | 11% | 9% | 2% | 2%
Foreign body sensation in eyes | 10% | 5% | 16% | 14% | 13% | 10% | 7% | 5%
Eye irritation | 8% | 5% | 15% | 15% | 13% | 12% | 7% | 6%
Lacrimation increased | 5% | 4% | 14% | 12% | 8% | 8% | 2% | 3%
Blepharitis | 3% | 2% | 12% | 8% | 8% | 5% | 0% | 1%
Dry eye | 5% | 3% | 12% | 7% | 7% | 7% | 3% | 3%
Visual disturbance or vision blurred | 8% | 4% | 18% | 15% | 13% | 10% | 5% | 3%
Eye pruritis | 4% | 4% | 12% | 11% | 9% | 7% | 1% | 2%
Ocular hyperemia | 9% | 9% | 11% | 8% | 7% | 4% | 5% | 3%
Retinal disorder | 2% | 2% | 10% | 7% | 8% | 4% | 2% | 1%
Maculopathy | 5% | 7% | 9% | 9% | 6% | 6% | 11% | 7%
Retinal degeneration | 1% | 0% | 8% | 6% | 5% | 3% | 1% | 0%
Ocular discomfort | 2% | 1% | 7% | 4% | 5% | 2% | 2% | 2%
Conjunctival hyperemia | 1% | 2% | 7% | 6% | 5% | 4% | 0% | 0%
Posterior capsule opacification | 4% | 3% | 7% | 4% | 2% | 2% | 0% | 1%
Injection site hemorrhage | 1% | 0% | 5% | 2% | 3% | 1% | 0% | 0%

Non-Ocular Reactions

Non-ocular adverse reactions with an incidence of ≥ 5% in patients receiving ranibizumab for DR, DME, AMD, and/or RVO and which occurred at a ≥ 1% higher frequency in patients treated with ranibizumab compared to control are shown in Table 2. Though less common, wound healing complications were also observed in some studies.

Table 2 Non-Ocular Reactions in the DME and DR, AMD, and RVO Studies
Adverse Reaction | DME and DR 2-year |  | AMD 2-year |  | AMD 1-year |  | RVO 6-month
Adverse Reaction | Ranibizumab 0.3 mg | Control | Ranibizumab 0.5 mg | Control | Ranibizumab 0.5 mg | Control | Ranibizumab 0.5 mg | Control
Adverse Reaction | n=250 | n=250 | n=379 | n=379 | n=440 | n=441 | n=259 | n=260
Nasopharyngitis | 12% | 6% | 16% | 13% | 8% | 9% | 5% | 4%
Anemia | 11% | 10% | 8% | 7% | 4% | 3% | 1% | 1%
Nausea | 10% | 9% | 9% | 6% | 5% | 5% | 1% | 2%
Cough | 9% | 4% | 9% | 8% | 5% | 4% | 1% | 2%
Constipation | 8% | 4% | 5% | 7% | 3% | 4% | 0% | 1%
Seasonal allergy | 8% | 4% | 4% | 4% | 2% | 2% | 0% | 2%
Hypercholesterolemia | 7% | 5% | 5% | 5% | 3% | 2% | 1% | 1%
Influenza | 7% | 3% | 7% | 5% | 3% | 2% | 3% | 2%
Renal failure | 7% | 6% | 1% | 1% | 0% | 0% | 0% | 0%
Upper respiratory tract infection | 7% | 7% | 9% | 8% | 5% | 5% | 2% | 2%
Gastroesophageal reflux disease | 6% | 4% | 4% | 6% | 3% | 4% | 1% | 0%
Headache | 6% | 8% | 12% | 9% | 6% | 5% | 3% | 3%
Edema peripheral | 6% | 4% | 3% | 5% | 2% | 3% | 0% | 1%
Renal failure chronic | 6% | 2% | 0% | 1% | 0% | 0% | 0% | 0%
Neuropathy peripheral | 5% | 3% | 1% | 1% | 1% | 0% | 0% | 0%
Sinusitis | 5% | 8% | 8% | 7% | 5% | 5% | 3% | 2%
Bronchitis | 4% | 4% | 11% | 9% | 6% | 5% | 0% | 2%
Atrial fibrillation | 3% | 3% | 5% | 4% | 2% | 2% | 1% | 0%
Arthralgia | 3% | 3% | 11% | 9% | 5% | 5% | 2% | 1%
Chronic obstructive pulmonary disease | 1% | 1% | 6% | 3% | 3% | 1% | 0% | 0%
Wound healing complications | 1% | 0% | 1% | 1% | 1% | 0% | 0% | 0%

6.3 Immunogenicity

The observed incidence of anti-drug antibodies is highly dependent on the sensitivity and specificity of the assay. Differences in assay methods preclude meaningful comparisons of the incidence of anti-drug antibodies in the studies described below with the incidence of anti-drug antibodies in other studies, including those of ranibizumab or of other ranibizumab products.

The pre-treatment incidence of immunoreactivity to ranibizumab was 0%-5% across treatment groups. After monthly dosing with ranibizumab for 6 to 24 months, antibodies to ranibizumab were detected in approximately 1%-9% of patients.

The clinical significance of immunoreactivity to ranibizumab products is unclear at this time. Among neovascular AMD patients with the highest levels of immunoreactivity, some were noted to have iritis or vitritis. Intraocular inflammation was not observed in patients with DME and DR at baseline, or RVO patients with the highest levels of immunoreactivity.

6.4 Postmarketing Experience

The following adverse reaction has been identified during post-approval use of ranibizumab products. Because this reaction was reported voluntarily from a population of uncertain size, it is not always possible to reliably estimate the frequency or establish a causal relationship to drug exposure.

- Ocular: Tear of retinal pigment epithelium among patients with neovascular AMD

7 DRUG INTERACTIONS

Drug interaction studies have not been conducted with ranibizumab products.

Ranibizumab intravitreal injection has been used adjunctively with PDT. Twelve of 105 (11%) patients with neovascular AMD developed serious intraocular inflammation; in 10 of the 12 patients, this occurred when ranibizumab was administered 7 days (± 2 days) after PDT.

8 USE IN SPECIFIC POPULATIONS

8.1 Pregnancy

Risk Summary

There are no adequate and well-controlled studies of ranibizumab products administered in pregnant women.

Administration of ranibizumab to pregnant monkeys throughout the period of organogenesis resulted in a low incidence of skeletal abnormalities at intravitreal doses 13-times the predicted human exposure (based on maximal serum trough levels [Cmax]) after a single eye treatment at the recommended clinical dose. No skeletal abnormalities were observed at serum trough levels equivalent to the predicted human exposure after a single eye treatment at the recommended clinical dose [see Animal Data] .

Animal reproduction studies are not always predictive of human response, and it is not known whether ranibizumab products can cause fetal harm when administered to a pregnant woman. Based on the anti-VEGF mechanism of action for ranibizumab products [see Clinical Pharmacology (12.1)] , treatment with ranibizumab products may pose a risk to human embryofetal development.

CIMERLI should be given to a pregnant woman only if clearly needed.

Data

Animal Data

An embryo-fetal developmental toxicity study was performed on pregnant cynomolgus monkeys. Pregnant animals received intravitreal injections of ranibizumab every 14 days starting on Day 20 of gestation, until Day 62 at doses of 0, 0.125, and 1 mg/eye. Skeletal abnormalities including incomplete and/or irregular ossification of bones in the skull, vertebral column, and hindlimbs and shortened supernumerary ribs were seen at a low incidence in fetuses from animals treated with 1 mg/eye of ranibizumab. The 1 mg/eye dose resulted in trough serum ranibizumab levels up to 13 times higher than predicted Cmax levels with single eye treatment in humans. No skeletal abnormalities were seen at the lower dose of 0.125 mg/eye, a dose which resulted in trough exposures equivalent to single eye treatment in humans. No effect on the weight or structure of the placenta, maternal toxicity, or embryotoxicity was observed.

8.2 Lactation

Risk Summary

There are no data available on the presence of ranibizumab products in human milk, the effects of ranibizumab products on the breastfed infant or the effects of ranibizumab products on milk production/excretion.

Because many drugs are excreted in human milk, and because the potential for absorption and harm to infant growth and development exists, caution should be exercised when CIMERLI is administered to a nursing woman.

The developmental and health benefits of breastfeeding should be considered along with the mother's clinical need for CIMERLI and any potential adverse effects on the breastfed child from CIMERLI.

8.3 Females and Males of Reproductive Potential

Infertility

No studies on the effects of ranibizumab products on fertility have been conducted and it is not known whether ranibizumab products can affect reproduction capacity. Based on the anti-VEGF mechanism of action for ranibizumab products, treatment with ranibizumab products may pose a risk to reproductive capacity.

8.4 Pediatric Use

The safety and effectiveness of CIMERLI in pediatric patients have not been established.

8.5 Geriatric Use

In the clinical studies, approximately 76% (2449 of 3227) of patients randomized to treatment with ranibizumab were ≥ 65 years of age and approximately 51% (1644 of 3227) were ≥ 75 years of age [see Clinical Studies (14)] . No notable differences in efficacy or safety were seen with increasing age in these studies. Age did not have a significant effect on systemic exposure.

10 OVERDOSAGE

More concentrated doses as high as 2 mg ranibizumab in 0.05 mL have been administered to patients. No additional unexpected adverse reactions were seen.

11 DESCRIPTION

Ranibizumab-eqrn is a recombinant humanized IgG1 kappa isotype monoclonal antibody fragment designed for intraocular use. Ranibizumab-eqrn binds to and inhibits the biologic activity of human vascular endothelial growth factor A (VEGF-A). Ranibizumab-eqrn, which lacks an Fc region, has a molecular weight of approximately 48 kilodaltons and is produced by an E. coli expression system.

CIMERLI (ranibizumab-eqrn) injection is a sterile, colorless to pale yellow solution in a single-dose glass vial for intravitreal injection. CIMERLI is supplied as a preservative-free, sterile solution in a single-dose container designed to deliver 0.05 mL of 10 mg/mL ranibizumab-eqrn (0.5 mg dose vial) or 6 mg/mL ranibizumab-eqrn (0.3 mg dose vial) aqueous solution with 10 mM histidine HCl, 10% α,α trehalose dihydrate, 0.01% polysorbate 20, pH 5.5.

12 CLINICAL PHARMACOLOGY

12.1 Mechanism of Action

Ranibizumab products bind to the receptor binding site of active forms of VEGF-A, including the biologically active, cleaved form of this molecule, VEGF110. VEGF-A has been shown to cause neovascularization and leakage in models of ocular angiogenesis and vascular occlusion and is thought to contribute to pathophysiology of neovascular AMD, mCNV, DR, DME and macular edema following RVO. The binding of ranibizumab products to VEGF-A prevents the interaction of VEGF-A with its receptors (VEGFR1 and VEGFR2) on the surface of endothelial cells, reducing endothelial cell proliferation, vascular leakage, and new blood vessel formation.

12.2 Pharmacodynamics

Increased retinal thickness (i.e., center point thickness (CPT) or central foveal thickness (CFT)), as assessed by optical coherence tomography (OCT) is associated with neovascular AMD, mCNV, macular edema following RVO, and DME. Leakage from choroidal neovascularization (CNV) as assessed by fluorescein angiography (FA) is associated with neovascular AMD and mCNV. Microvascular retinal changes and neovascularization, as assessed by color fundus photography, are associated with diabetic retinopathy.

Neovascular (Wet) Age-Related Macular Degeneration

In Study AMD-3, CPT was assessed by time domain (TD)-OCT in 118 of 184 patients. TD-OCT measurements were collected at baseline, Months 1, 2, 3, 5, 8, and 12. In patients treated with ranibizumab, CPT decreased, on average, more than in the sham group from baseline through Month 12. CPT decreased by Month 1 and decreased further at Month 3, on average. In this study, CPT data did not provide information useful in influencing treatment decisions [see Clinical Studies (14.1)] .

In Study AMD-4, CFT was assessed by spectral domain (SD)-OCT in all patients; on average, CFT reductions were observed beginning at Day 7 following the first ranibizumab injection through Month 24. CFT data did not provide information capable of predicting final visual acuity results [see Clinical Studies (14.1)] .

In patients treated with ranibizumab, the area of CNV leakage, on average, decreased by Month 3 as assessed by FA. The area of CNV leakage for an individual patient was not correlated with visual acuity.

Macular Edema Following Retinal Vein Occlusion

On average, CPT reductions were observed in Studies RVO-1 and RVO-2 beginning at Day 7 following the first ranibizumab injection through Month 6. CPT was not evaluated as a means to guide treatment decisions [see Clinical Studies (14.2)] .

Diabetic Macular Edema

On average, CPT reductions were observed in Studies D-1 and D-2 beginning at Day 7 following the first ranibizumab injection through Month 36. CPT data did not provide information useful in influencing treatment decisions [see Clinical Studies (14.3)] .

Diabetic Retinopathy

Improvements from baseline in DR severity as assessed on fundus photography were observed in Studies D-1 and D-2 at Month 3 (first scheduled DR photographic assessment after randomization) through Month 36 [see Clinical Studies (14.4)] .

Myopic Choroidal Neovascularization

On average CFT reductions were observed as early as Month 1, and were greater in the ranibizumab groups compared to PDT [see Clinical Studies (14.5)] .

12.3 Pharmacokinetics

In patients with neovascular AMD, following monthly intravitreal administration of 0.5 mg ranibizumab, mean (±SD) maximum ranibizumab serum concentrations were 1.7 (± 1.1) ng/mL. These concentrations were below the concentration range of ranibizumab (11 to 27 ng/mL) that was necessary to inhibit the biological activity of VEGF-A by 50%, as measured in an in vitro cellular proliferation assay (based on human umbilical vein endothelial cells (HUVEC)). No significant change from baseline was observed in the mean plasma VEGF concentrations following three monthly 0.5 mg intravitreal injections. The maximum observed serum concentration was dose proportional over the dose range of 0.05 to 2 mg/eye. Serum ranibizumab concentrations in RVO and DME and DR patients were similar to those observed in neovascular AMD patients.

Based on a population pharmacokinetic analysis of patients with neovascular AMD, maximum serum concentrations are predicted to be reached at approximately 1 day after monthly intravitreal administration of ranibizumab 0.5 mg/eye. Based on the disappearance of ranibizumab from serum, the estimated average vitreous elimination half-life was approximately 9 days. Steady-state minimum concentration is predicted to be 0.22 ng/mL with a monthly dosing regimen. In humans, serum ranibizumab concentrations are predicted to be approximately 90,000-fold lower than vitreal concentrations.

In pharmacokinetic covariate analyses, 48% (520/1091) of patients had renal impairment (35% mild, 11% moderate, and 2% severe). Because the increases in plasma ranibizumab exposures in these patients are not considered clinically significant, no dosage adjustment is needed based on renal impairment status.

13 NONCLINICAL TOXICOLOGY

13.1 Carcinogenesis, Mutagenesis, Impairment of Fertility

Animal studies have not been conducted to determine the carcinogenic potential of ranibizumab products. Based on the anti-VEGF mechanism of action of ranibizumab products, treatment with ranibizumab products may pose a risk to reproductive capacity [see Females and Males of Reproductive Potential (8.3)] .

14 CLINICAL STUDIES

Unless otherwise noted, visual acuity was measured at a distance of 4 meters.

14.1 Neovascular (Wet) Age-Related Macular Degeneration (AMD)

The safety and efficacy of ranibizumab were assessed in three randomized, double-masked, sham- or active-controlled studies in patients with neovascular AMD. A total of 1323 patients (ranibizumab 879, control 444) were enrolled in the three studies.

Studies AMD-1 and AMD-2

In Study AMD-1, patients with minimally classic or occult (without classic) CNV lesions received monthly ranibizumab 0.3 mg or 0.5 mg intravitreal injections or monthly sham injections. Data are available through Month 24. Patients treated with ranibizumab in Study AMD-1 received a mean of 22 total treatments out of a possible 24 from Day 0 to Month 24.

In Study AMD-2, patients with predominantly classic CNV lesions received one of the following: 1) monthly ranibizumab 0.3 mg intravitreal injections and sham PDT; 2) monthly ranibizumab 0.5 mg intravitreal injections and sham PDT; or 3) sham intravitreal injections and active PDT. Sham PDT (or active PDT) was given with the initial ranibizumab (or sham) intravitreal injection and every 3 months thereafter if FA showed persistence or recurrence of leakage. Data are available through Month 24. Patients treated with ranibizumab in Study AMD-2 received a mean of 21 total treatments out of a possible 24 from Day 0 through Month 24.

In both studies, the primary efficacy endpoint was the proportion of patients who maintained vision, defined as losing fewer than 15 letters of visual acuity at 12 months compared with baseline. Almost all ranibizumab-treated patients (approximately 95%) maintained their visual acuity. Among ranibizumab-treated patients, 31% to 37% experienced a clinically significant improvement in vision, defined as gaining 15 or more letters at 12 months. The size of the lesion did not significantly affect the results. Detailed results are shown in Table 3, Table 4, and Figure 1 below.

Table 3 Visual Acuity Outcomes at Month 12 and Month 24 in Study AMD-1
Outcome Measure | Month | Sham n=229 | Ranibizumab 0.5 mg n=230 | Estimated Difference (95% CI) [Adjusted estimate based on the stratified model; p < 0.01]
Loss of <15 letters in visual acuity (%) | 12 | 60% | 91% | 30% (23%, 37%)
 | 24 | 56% | 89% | 33% (26%, 41%)
Gain of ≥15 letters in visual acuity (%) | 12 | 6% | 31% | 25% (18%, 31%)
 | 24 | 4% | 30% | 25% (18%, 31%)
Mean change in visual acuity (letters) (SD) | 12 | −11.0 (17.9) | +6.3 (14.1) | 17.1 (14.2, 20.0)
 | 24 | −15.0 (19.7) | +5.5 (15.9) | 20.1 (16.9, 23.4)

Table 4 Visual Acuity Outcomes at Month 12 and Month 24 in Study AMD-2
Outcome Measure | Month | PDT n=141 | Ranibizumab 0.5 mg n=139 | Estimated Difference (95% CI) [Adjusted estimate based on the stratified model; p < 0.01]
Loss of <15 letters in visual acuity (%) | 12 | 66% | 98% | 32% (24%, 40%)
 | 24 | 65% | 93% | 28% (19%, 37%)
Gain of ≥15 letters in visual acuity (%) | 12 | 11% | 37% | 26% (17%, 36%)
 | 24 | 9% | 37% | 29% (20%, 39%)
Mean change in visual acuity (letters) (SD) | 12 | −8.5 (17.8) | +11.0 (15.8) | 19.8 (15.9, 23.7)
 | 24 | −9.1 (18.7) | +10.9 (17.3) | 20 (16.0, 24.4)

Figure 1
Mean Change in Visual Acuity [Visual acuity was measured at a distance of 2 meters] from Baseline to Month 24 in Study AMD-1 and Study AMD-2

Patients in the group treated with ranibizumab had minimal observable CNV lesion growth, on average. At Month 12, the mean change in the total area of the CNV lesion was 0.1-0.3 disc areas (DA) for ranibizumab versus 2.3-2.6 DA for the control arms. At Month 24, the mean change in the total area of the CNV lesion was 0.3-0.4 DA for ranibizumab versus 2.9-3.1 DA for the control arms.

Study AMD-3

Study AMD-3 was a randomized, double-masked, sham-controlled, 2-year study designed to assess the safety and efficacy of ranibizumab in patients with neovascular AMD (with or without a classic CNV component). Data are available through Month 12. Patients received ranibizumab 0.3 mg or 0.5 mg intravitreal injections or sham injections once a month for three consecutive doses, followed by a dose administered once every 3 months for 9 months. A total of 184 patients were enrolled in this study (ranibizumab 0.3 mg, 60; ranibizumab 0.5 mg, 61; sham, 63); 171 (93%) completed 12 months of this study. Patients treated with ranibizumab in Study AMD-3 received a mean of six total treatments out of a possible 6 from Day 0 through Month 12.

In Study AMD-3, the primary efficacy endpoint was the mean change in visual acuity at 12 months compared with baseline (see Figure 2). After an initial increase in visual acuity (following monthly dosing), on average, patients dosed once every 3 months with ranibizumab lost visual acuity, returning to baseline at Month 12. In Study AMD-3, almost all ranibizumab-treated patients (90%) lost fewer than 15 letters of visual acuity at Month 12.

Figure 2
Mean Change in Visual Acuity from Baseline to Month 12 in Study AMD-3

Study AMD-4

Study AMD-4 was a randomized, double-masked, active treatment-controlled, two-year study designed to assess the safety and efficacy of ranibizumab 0.5 mg administered monthly or less frequently than monthly in patients with neovascular AMD. Patients randomized to the ranibizumab 0.5 mg less frequent dosing arm received three monthly doses followed by monthly assessments where patients were eligible to receive ranibizumab injections guided by pre-specified re-treatment criteria. A total of 550 patients were enrolled in the two 0.5 mg treatment groups with 467 (85%) completing through Month 24. Data are available through Month 24.

Clinical results at Month 24 remain similar to that observed at Month 12.

From Month 3 through Month 24, visual acuity decreased by 0.3 letters in the 0.5 mg less frequent dosing arm and increased by 0.7 letters in the 0.5 mg monthly arm (see Figure 3). Over this 21-month period, patients in the 0.5 mg less frequent dosing and the 0.5 mg monthly arms averaged 10.3 and 18.5 injections, respectively. The distribution of injections received in the less frequent dosing arm is shown in Figure 4.

Figure 3
Mean Change in Visual Acuity from Baseline to Month 24 in Study AMD-4

Figure 4
Distribution of Injections from Month 3 to Month 24 in the Less Frequent Dosing Arm in Study AMD-4

14.2 Macular Edema Following Retinal Vein Occlusion (RVO)

The safety and efficacy of ranibizumab were assessed in two randomized, double-masked, 1-year studies in patients with macular edema following RVO. Sham controlled data are available through Month 6. Patient age ranged from 20 to 91 years, with a mean age of 67 years. A total of 789 patients (ranibizumab 0.3 mg, 266 patients; ranibizumab 0.5 mg, 261 patients; sham, 262 patients) were enrolled, with 739 (94%) patients completing through Month 6. All patients completing Month 6 were eligible to receive ranibizumab injections guided by pre-specified re-treatment criteria until the end of the studies at Month 12.

In Study RVO-1, patients with macular edema following branch or hemi-RVO, received monthly ranibizumab 0.3 mg or 0.5 mg intravitreal injections or monthly sham injections for 6 months. All patients were eligible for macular focal/grid laser treatment beginning at Month 3 of the 6-month treatment period. Macular focal/grid laser treatment was given to 26 of 131 (20%) patients treated with 0.5 mg ranibizumab and 71 of 132 (54%) patients treated with sham.

In Study RVO-2, patients with macular edema following central RVO received monthly ranibizumab 0.3 mg or 0.5 mg intravitreal injections or monthly sham injections for 6 months.

At Month 6, after monthly treatment with 0.5 mg ranibizumab, the following clinical results were observed:

Table 5 Visual Acuity Outcomes at Month 6 in Study RVO-1 and Study RVO-2
Outcome Measure | Study [RVO-1: Sham, n=131; ranibizumab 0.5 mg, n=132 RVO-2: Sham, n=130; ranibizumab 0.5 mg, n=130] | Sham | Ranibizumab 0.5 mg | Estimated Difference (95% CI) [Adjusted estimate based on stratified model; p < 0.01]
Gain of ≥15 letters in visual acuity (%) | RVO-1 | 29% | 61% | 31% (20%, 43%)
Gain of ≥15 letters in visual acuity (%) | RVO-2 | 17% | 48% | 30% (20%, 41%)

Figure 5
Mean Change in Visual Acuity from Baseline to Month 6 in Study RVO-1 and Study RVO-2

14.3 Diabetic Macular Edema (DME)

Efficacy and safety data of ranibizumab are derived from studies D-1 and D-2 [see Clinical Studies (14.4)] . All enrolled patients had DR and DME at baseline.

The safety and efficacy of ranibizumab were assessed in two randomized, double-masked, 3-year studies. The studies were sham-controlled through Month 24. Patient age ranged from 21 to 91 years, with a mean age of 62 years. A total of 759 patients (ranibizumab 0.3 mg, 250 patients; ranibizumab 0.5 mg, 252 patients; sham, 257 patients) were enrolled, with 582 (77%) completing through Month 36.

In Studies D-1 and D-2, patients received monthly ranibizumab 0.3 mg or 0.5 mg intravitreal injections or monthly sham injections during the 24-month controlled treatment period. From Months 25 through 36, patients who previously received sham were eligible to receive monthly ranibizumab 0.5 mg and patients originally randomized to monthly ranibizumab 0.3 mg or 0.5 mg continued to receive their assigned dose. All patients were eligible for macular focal/grid laser treatment beginning at Month 3 of the 24-month treatment period or panretinal photocoagulation (PRP) as needed. Through Month 24, macular focal/grid laser treatment was administered in 94 of 250 (38%) patients treated with ranibizumab 0.3 mg and 185 of 257 (72%) patients treated with sham; PRP was administered in 2 of 250 (1%) patients treated with ranibizumab 0.3 mg and 30 of 257 (12%) patients treated with sham.

Compared to monthly ranibizumab 0.3 mg, no additional benefit was observed with monthly treatment with ranibizumab 0.5 mg. At Month 24, after monthly treatment with ranibizumab 0.3 mg, the following clinical results were observed:

Table 6 Visual Acuity Outcomes at Month 24 in Study D-1 and D-2
Outcome Measure | Study [D-1: Sham, n=130; ranibizumab 0.3 mg, n=125 D-2: Sham, n=127; ranibizumab 0.3 mg, n=125] | Sham | Ranibizumab 0.3 mg | Estimated Difference (95% CI) [Adjusted estimate based on stratified model; p ≤ 0.01]
Gain of ≥15 letters in visual acuity (%) | D-1 | 12% | 34% | 21% (11%, 30%)
Gain of ≥15 letters in visual acuity (%) | D-2 | 18% | 45% | 24% (14%, 35%)
Loss of <15 letters in visual acuity (%) | D-1 | 92% | 98% | 7% (2%, 13%)
Loss of <15 letters in visual acuity (%) | D-2 | 90% | 98% | 8% (2%, 14%)
Mean change in visual acuity (letters) | D-1 | 2.3 | 10.9 | 8.5 (5.4, 11.5)
Mean change in visual acuity (letters) | D-2 | 2.6 | 12.5 | 9.6 (6.1, 13.0)

Figure 6
Mean Change in Visual Acuity from Baseline to Month 36 in Study D-1 and Study D-2

p < 0.01 for all time points comparing ranibizumab 0.3 mg to sham through Month 24

Visual acuity outcomes observed at Month 24 in patients treated with ranibizumab 0.3 mg were maintained with continued treatment through Month 36 in both DME studies. Patients in the sham arms who received ranibizumab 0.5 mg beginning at Month 25 achieved lesser VA gains compared to patients who began treatment with ranibizumab at the beginning of the studies.

In Studies D-1 and D-2, patients received monthly injections of ranibizumab for 12 or 36 months, after which 500 patients opted to continue in the long-term follow-up study. Of 298 patients who had at least 12 months of follow-up from Month 36, 58 (19.5%) patients maintained vision with no further therapy. The remaining 202 patients were followed for less than 12 months.

14.4 Diabetic Retinopathy (DR)

Efficacy and safety data of ranibizumab are derived from Studies D-1 and D-2 [see Clinical Studies (14.3)] and D-3. All enrolled patients in Studies D-1 and D-2 had DR and DME at baseline. Study D-3 enrolled DR patients both with and without DME at baseline.

Of the 759 patients enrolled in Studies D-1 and D-2, 746 patients had a baseline assessment of fundus photography. Patients had baseline Early Treatment Diabetic Retinopathy Study Diabetic Retinopathy Severity Scores (ETDRS-DRSS) ranging from 10 to 75. At baseline, 62% of patients had non-proliferative diabetic retinopathy (NPDR) (ETDRS-DRSS less than 60) and 31% had proliferative diabetic retinopathy (PDR) (ETDRS-DRSS greater than or equal to 60). The ETDRS-DRSS could not be graded in 5% of patients at baseline, and 2% of patients had absent or questionable DR at baseline. Approximately 20% of the overall population had prior PRP.

After monthly treatment with ranibizumab 0.3 mg, the following clinical results were observed (Table 7; Figure 7):

Table 7 ≥3-Step and ≥2-Step Improvement at Month 24 in Study D-1 and Study D-2
Outcome Measure | Study [D-1: Sham, n=124; ranibizumab 0.3 mg, n=117 D-2: Sham, n=115; ranibizumab 0.3 mg, n=117] | Sham | Ranibizumab 0.3 mg | Estimated Difference (95% CI) [Adjusted estimate based on stratified model]
≥3-step improvement from baseline in ETDRS-DRSS [p < 0.05 for all time points comparing ranibizumab 0.3 mg to sham from Month 12 through Month 24] | D-1 | 2% | 17% | 15% (7%, 22%)
≥3-step improvement from baseline in ETDRS-DRSS [p < 0.05 for all time points comparing ranibizumab 0.3 mg to sham from Month 12 through Month 24] | D-2 | 0% | 9% | 9% (4%, 14%)
≥2-step improvement from baseline in ETDRS-DRSS [p < 0.05 for all time points comparing ranibizumab 0.3 mg to sham from Month 3 through Month 24] | D-1 | 4% | 39% | 35% (26%, 44%)
≥2-step improvement from baseline in ETDRS-DRSS [p < 0.05 for all time points comparing ranibizumab 0.3 mg to sham from Month 3 through Month 24] | D-2 | 7% | 37% | 31% (21%, 40%)

At Month 24, DR improvement by ≥3-steps in ETDRS-DRSS from baseline in subgroups examined (e.g., age, gender, race, baseline visual acuity, baseline HbA1c, prior DME therapy at baseline, baseline DR severity (NPDR, PDR)) were generally consistent with the results in the overall population.

The difference in the proportion of patients treated with ranibizumab 0.3 mg compared to sham who achieved DR improvement based on the ETDRS-DRSS was observed as early as Month 3 for ≥2-step improvement or at Month 12 for ≥3-step improvement.

Figure 7
Proportion of Patients with ≥ 3-Step and ≥ 2-Step Improvement from Baseline in ETDRS Diabetic Retinopathy Severity Level over Time in Study D-1 and Study D-2

Study D-3 enrolled DR patients with and without DME; 88 (22%) eyes with baseline DME and 306 (78%) eyes without baseline DME and balanced across treatment groups. Study D-3 was a randomized, active-controlled study where patient age ranged from 20 to 83 with a mean age of 51 years. A total of 394 study eyes from 305 patients, including 89 who had both eyes randomized, were enrolled (ranibizumab, 191 study eyes; pan-retinal photocoagulation; 203 study eyes). All eyes in the ranibizumab group received a baseline 0.5 mg intravitreal injection followed by 3 monthly intravitreal injections, after which treatment was guided by pre-specified retreatment criteria. Patients had baseline ETDRS-DRSS ranging from 20 to 85. At baseline, 11% of eyes had NPDR (ETDRS-DRSS less than 60), 50% had mild-to-moderate PDR (ETDRS-DRSS equal to 60, 61, or 65), and 37% had high-risk PDR (ETDRS-DRSS greater than or equal to 71).

An analysis of data from Study D-3 demonstrated that at Year 2 in the ranibizumab group, 31.7% and 28.4% of eyes in the subgroups with baseline DME and without baseline DME, respectively, had ≥ 3-step improvement from baseline in ETDRS-DRSS.

Table 8 Proportion of Eyes with ≥ 3-Step and ≥ 2-Step Improvement from Baseline in ETDRS-DRSS at Year 2 in Study D-3
 | Ranibizumab group
Outcome Measure (in ETDRS-DRSS) | Eyes with Baseline DME n = 41 | Eyes without Baseline DME n = 148
≥ 3-step improvement from baseline 95% CI for percentage | 13 (31.7%) (17.5%, 46.0%) | 42 (28.4%) (21.1%, 35.6%)
≥ 2-step improvement from baseline 95% CI for percentage | 24 (58.5%) (43.5%, 73.6%) | 56 (37.8%) (30.0%, 45.7%)

Figure 8
Proportion of Eyes in the ranibizumab group with ≥ 3-Step and ≥ 2-Step Improvement from Baseline in ETDRS-DRSS at Year 1 and Year 2 in Study D-3

14.5 Myopic Choroidal Neovascularization (mCNV)

The efficacy and safety data of ranibizumab were assessed in a randomized, double-masked, active-controlled 3-month study in patients with mCNV. Patients age ranged from 18 to 87 years, with a mean age of 55 years. A total of 276 patients (222 patients in the ranibizumab treated Groups I and II; 55 patients in the active control PDT group) were enrolled. Patients randomized to the ranibizumab groups received injections guided by prespecified re-treatment criteria. The retreatment criteria in Group I were vision stability guided, with the Best Corrected Visual Acuity (BCVA) at the current visit being assessed for changes compared with the two preceding monthly BCVA values. The retreatment criteria in Group II were disease activity guided, based on BCVA decrease from the previous visit that was attributable to intra- or sub-retinal fluid or active leakage secondary to mCNV as assessed by OCT and/or FA compared to the previous monthly visit.

Visual gains for the two ranibizumab 0.5 mg treatment arms were superior to the active control arm. The mean change in BCVA from baseline at Month 3 was: +12.1 letters for Group I, +12.5 letters for Group II and +1.4 letters for the PDT group. (Figure 9; Table 9). Efficacy was comparable between Group I and Group II.

Table 9 Mean Change in Visual Acuity and Proportion of Patients who Gained ≥15 letters from Baseline at Month 3
Study Arms | Mean change in BCVA from baseline (Letters) |  | Proportion of patients who gained ≥15 letters from baseline
Study Arms | Mean (SD) | Estimated Difference (95% CI) [Adjusted estimates based on stratified models; p < 0.01] | Percent | Estimated Difference (95% CI)
Group I | 12.1 (10.2) | 10.9 (7.6, 14.3) | 37.1 | 22.6 (9.5, 35.7)
Group II | 12.5 (8.8) | 11.4 (8.3, 14.5) | 40.5 | 26.0 (13.1, 38.9)
Control (PDT) | 1.4 (12.2) |  | 14.5

Figure 9
Mean Change in Visual Acuity from Baseline to Month 3 in mCNV Study

The proportion of patients who gained ≥15 letters (ETDRS) by Month 3 was 37.1% and 40.5% for ranibizumab Groups I and II, respectively and 14.5% for the PDT group. The mean number of injections between baseline and Month 3 was 2.5 and 1.8 for Groups I and II, respectively. 41% of patients received 1, 2 or 3 injections between baseline and Month 3 with no injections afterwards.

16 HOW SUPPLIED/STORAGE AND HANDLING

CIMERLI (ranibizumab-eqrn) injection is a colorless to pale yellow solution supplied in:

- Each CIMERLI 0.5 mg carton (NDC 70114-441-01) contains a single-dose, 2-mL glass vial with a BLUE CAP designed to deliver 0.05 mL of 10 mg/mL ranibizumab-eqrn solution.
- Each CIMERLI 0.3 mg carton (NDC 70114-440-01) contains a single-dose, 2-mL glass vial with a WHITE CAP designed to deliver 0.05 mL of 6 mg/mL ranibizumab-eqrn solution.

EACH CARTON IS FOR SINGLE-EYE USE ONLY.

STORAGE AND HANDLING

CIMERLI should be refrigerated at 2°C to 8°C (36°F to 46°F). DO NOT FREEZE. Do not use beyond the expiry date stamped on the label. Protect CIMERLI vials from light and store in the original carton until time of use.

17 PATIENT COUNSELING INFORMATION

Advise patients that in the days following CIMERLI administration, patients are at risk of developing endophthalmitis and retinal vasculitis with or without occlusion. If the eye becomes red, sensitive to light, painful, or develops a change in vision, advise the patient to seek immediate care from an ophthalmologist [see Warnings and Precautions (5.1, 5.5)] .

CIMERLI is a trademark of Coherus BioSciences, Inc.

Manufactured by:
Coherus BioSciences, Inc.
Redwood City, California, USA
US License No. 2023

PMD-0141, Rev 03

PRINCIPAL DISPLAY PANEL - 0.3 mg Vial Carton

NDC 70114-440-01

CIMERLI™
(ranibizumab-eqrn) injection

0.3 mg single-dose vial

For Intravitreal Use

Rx Only

Carton contents:

- One single-dose glass vial
- Prescribing information

Indicated for:

- Diabetic Macular Edema
- Diabetic Retinopathy

0.3 mg

Coherus™
BIOSCIENCES

PRINCIPAL DISPLAY PANEL - 0.5 mg Vial Carton

NDC 70114-441-01

CIMERLI™
(ranibizumab-eqrn) injection

0.5 mg single-dose vial

For Intravitreal Use

Rx Only

Carton contents:

- One single-dose glass vial
- Prescribing information

Indicated for:

- Neovascular (wet) age-related
  macular degeneration
- Macular edema following
  retinal vein occlusion
- Myopic choroidal
  neovascularization

0.5 mg

Coherus™
BIOSCIENCES